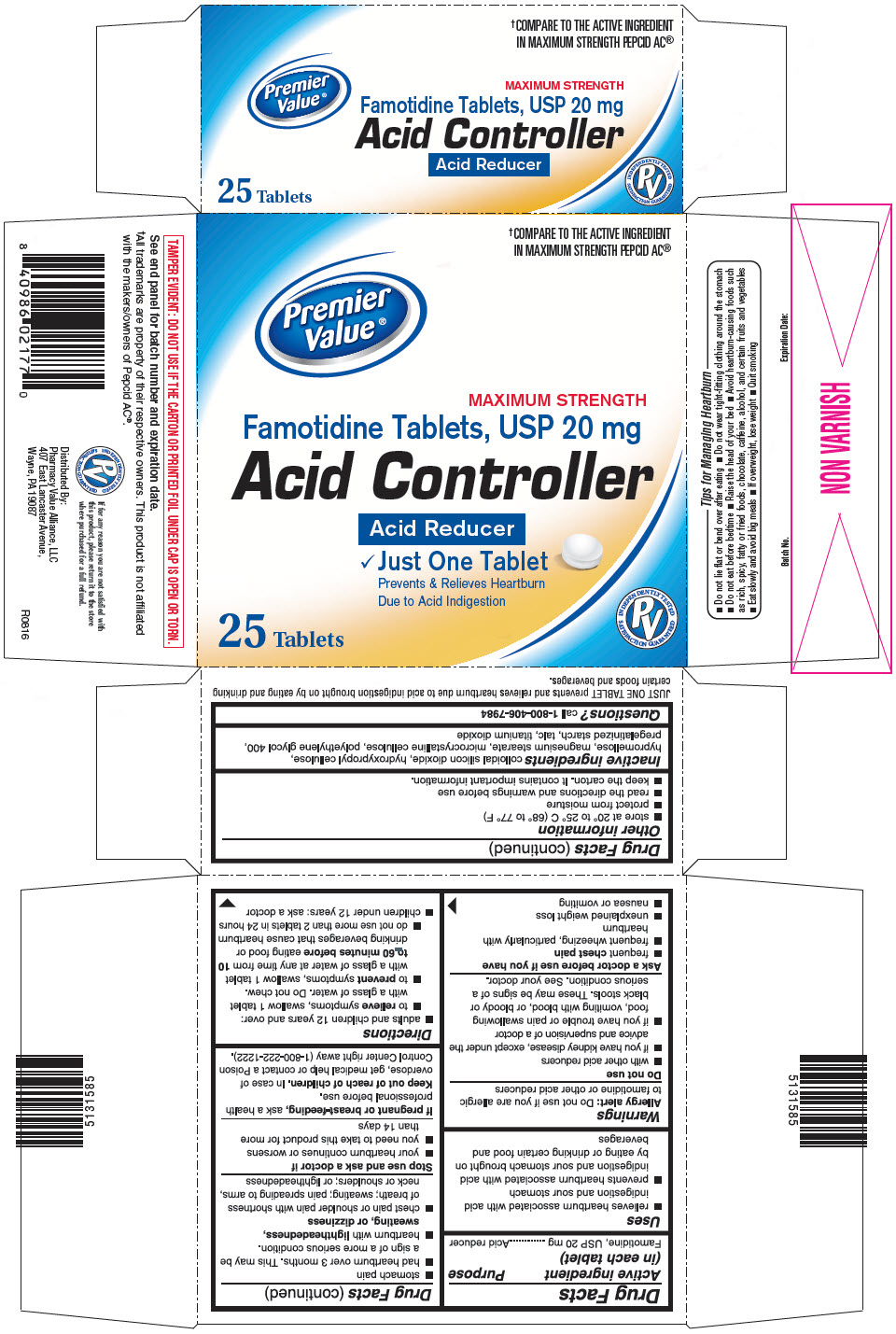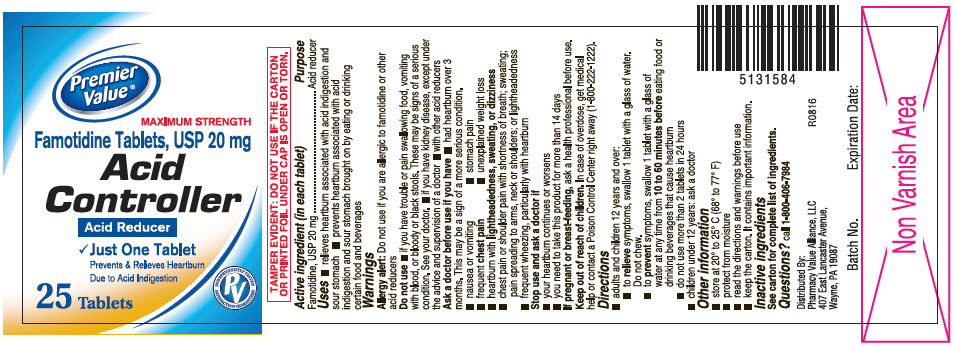 DRUG LABEL: Premier Value Famotidine
NDC: 68016-010 | Form: TABLET, FILM COATED
Manufacturer: Premier Value
Category: otc | Type: HUMAN OTC DRUG LABEL
Date: 20191227

ACTIVE INGREDIENTS: FAMOTIDINE 10 mg/1 1
INACTIVE INGREDIENTS: SILICON DIOXIDE; HYDROXYPROPYL CELLULOSE (1600000 WAMW); HYPROMELLOSE, UNSPECIFIED; FERRIC OXIDE RED; MAGNESIUM STEARATE; MICROCRYSTALLINE CELLULOSE; POLYETHYLENE GLYCOL 400; STARCH, CORN; TALC; TITANIUM DIOXIDE

Premier Value® Famotidine

Drug Facts

Active ingredient (in each tablet)

Famotidine, USP 20 mg

Purpose

Acid reducer

Uses

- relieves heartburn associated with acid indigestion and sour stomach
- prevents heartburn associated with acid indigestion and sour stomach brought on by eating or drinking certain food and beverages

Warnings

Allergy alert

Do not use if you are allergic to famotidine or other acid reducers

Do not use

- with other acid reducers
- if you have kidney disease, except under the advice and supervision of a doctor
- if you have trouble or pain swallowing food, vomiting with blood, or bloody or black stools. These may be signs of a serious condition. See your doctor.

Ask a doctor before use if you have

- frequent chest pain
- frequent wheezing, particularly with heartburn
- unexplained weight loss
- nausea or vomiting
- stomach pain
- had heartburn over 3 months. This may be a sign of a more serious condition.
- heartburn with lightheadedness, sweating, or dizziness
- chest pain or shoulder pain with shortness of breath; sweating; pain spreading to arms, neck or shoulders; or lightheadedness

Stop use and ask a doctor if

- your heartburn continues or worsens
- you need to take this product for more than 14 days

PREGNANCY OR BREAST FEEDING

If pregnant or breast-feeding, ask a health professional before use.

Keep out of reach of children. In case of overdose, get medical help or contact a Poison Control Center right away (1-800-222-1222).

Directions

- adults and children 12 years and over:
  - to relieve symptoms, swallow 1 tablet with a glass of water. Do not chew.
  - to prevent symptoms, swallow 1 tablet with a glass of water at any time from 10 to 60 minutes before eating food or drinking beverages that cause heartburn
  - do not use more than 2 tablets in 24 hours
- children under 12 years: ask a doctor

Other information

- store at 20° to 25° C (68° to 77° F)
- protect from moisture
- read the directions and warnings before use
- keep the carton. It contains important information.

Inactive ingredients

colloidal silicon dioxide, hydroxypropyl cellulose, hypromellose, magnesium stearate, microcrystalline cellulose, polyethylene glycol 400, pregelatinized starch, talc, titanium dioxide

Questions?

call 1-800-406-7984

Distributed By:
Pharmacy Value Alliance, LLC
407 East Lancaster Avenue,
Wayne, PA 19087

PRINCIPAL DISPLAY PANEL - 25 Tablet Bottle Carton

†COMPARE TO THE ACTIVE INGREDIENT
IN MAXIMUM STRENGTH PEPCID AC®

Premier
Value ®

MAXIMUM STRENGTH
Famotidine Tablets, USP 20 mg
Acid Controller

Acid Reducer

✓ Just One Tablet
  Prevents & Relieves Heartburn
  Due to Acid Indigestion

25 Tablets

INDEPENDENTLY TESTED
PV
SATISFACTION GUARANTEED

PRINCIPAL DISPLAY PANEL - 25 Tablet Bottle Label

Premier
Value ®

MAXIMUM STRENGTH
Famotidine Tablets, USP 20 mg
Acid
Controller

Acid Reducer

✓ Just One Tablet
  Prevents & Relieves Heartburn
  Due to Acid Indigestion

25 Tablets

INDEPENDENTLY TESTED
PV
SATISFACTION GUARANTEED